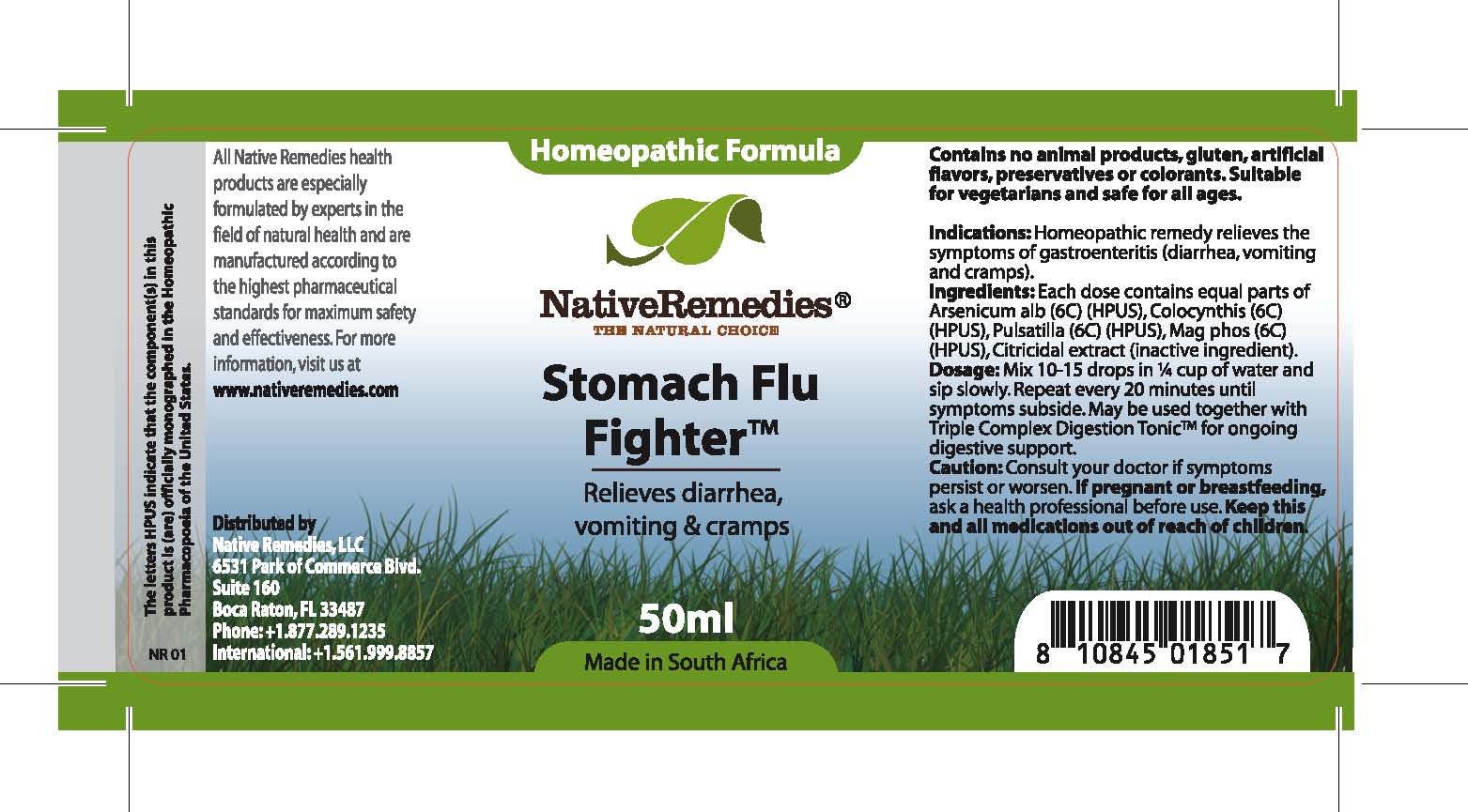 DRUG LABEL: Stomach Flu Fighter
NDC: 68647-202 | Form: TINCTURE
Manufacturer: Feelgood Health
Category: homeopathic | Type: HUMAN OTC DRUG LABEL
Date: 20100902

ACTIVE INGREDIENTS: ARSENIC TRIOXIDE 6 [hp_C]/50 mL; CITRULLUS COLOCYNTHIS FRUIT PULP 6 [hp_C]/50 mL; PULSATILLA PATENS 6 [hp_C]/50 mL; MAGNESIUM PHOSPHATE 6 [hp_C]/50 mL
INACTIVE INGREDIENTS: CITRUS PARADISI SEED 0.03 mL/50 mL; WATER 98.97 mL/50 mL

STOMACH FLU FIGHTER

PURPOSE

Relieves diarrhea, vomiting and cramps

INDICATIONS AND USAGE

Indications: Homeopathic remedy relieves the symptoms of gastroenteritis (diarrhea, vomiting and cramps).

DOSAGE AND ADMINISTRATION

Dosage: Mix 10-15 drops in ¼ cup of water and sip slowly. Repeat every 20 minutes until symptoms subside. May be used together with Triple Complex Digestion Tonic™ for ongoing digestive support.

GENERAL PRECAUTIONS

Caution: Consult your doctor if symptoms persist or worsen. Keep this and all medications out of reach of children.

ACTIVE INGREDIENT

Ingredients: Each dose contains equal parts of Arsenicum alb (6C) (HPUS), Colocynthis (6C) (HPUS), Pulsatilla (6C) (HPUS), Mag phos (6C) (HPUS)

Citricidal extract (inactive ingredient)

PREGNANCY

If pregnant or breastfeeding, ask a health professional before use.

WARNINGS

Contains no animal products, gluten, artificial flavors, preservatives or colorants. Suitable for vegetarians and safe for all ages.

PATIENT COUNSELING INFORMATION

All Native Remedies health products are especially formulated by experts in the field of natural health and are manufactured according to the highest pharmaceutical standards for maximum safety and effectiveness. For more information, visit us at www.nativeremedies.com

Distributed by

Native Remedies, LLC

6531 Park of Commerce Blvd.

Suite 160

Boca Raton, FL 33487

Phone: 1.877.289.1235

International: + 1.561.999.8857

The letters HPUS indicate that the component(s) in this product is (are) officially monographed in the Homeopathic Pharmacopoeia of the United States.

KEEP OUT OF REACH OF CHILDREN

Keep this and all medications out of reach of children.